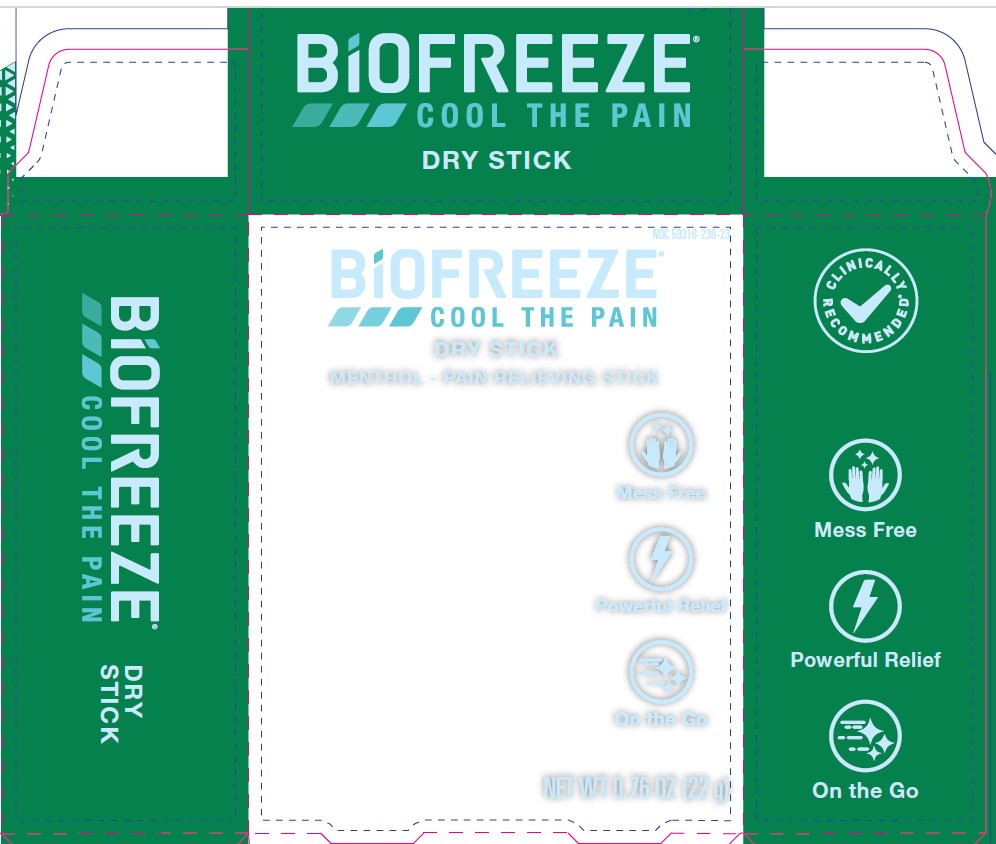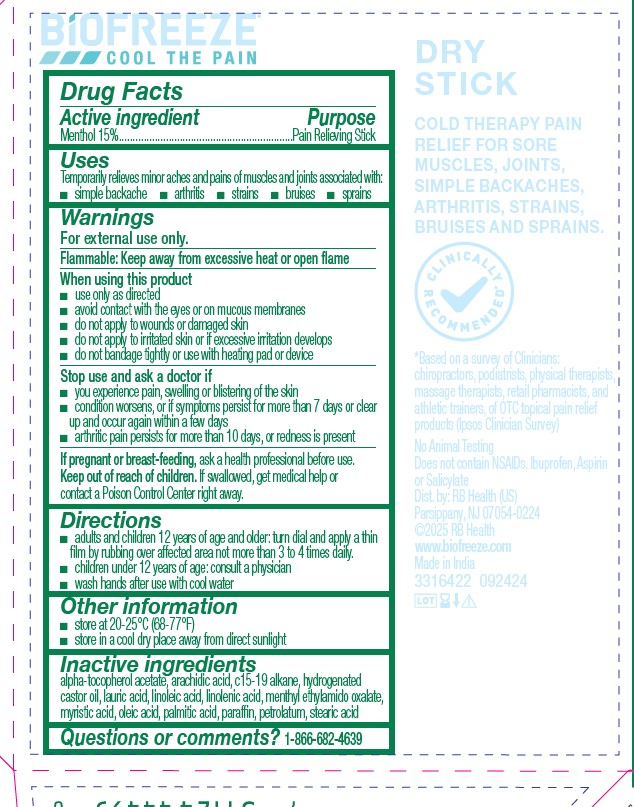 DRUG LABEL: BioFreeze Dry Stick
NDC: 59316-230 | Form: STICK
Manufacturer: RB Health (US) LLC
Category: otc | Type: HUMAN OTC DRUG LABEL
Date: 20241113

ACTIVE INGREDIENTS: MENTHOL 0.15 g/1 g
INACTIVE INGREDIENTS: ARACHIDIC ACID; C15-19 ALKANE; HYDROGENATED CASTOR OIL; OLEIC ACID; LINOLEIC ACID; PARAFFIN; MENTHYL ETHYLAMIDO OXALATE; PALMITIC ACID; MYRISTIC ACID; .ALPHA.-TOCOPHEROL ACETATE; STEARIC ACID; LAURIC ACID; LINOLENIC ACID; PETROLATUM

Biofreeze Dry Stick

Active ingredient:

Menthol 15%

Purpose:

Pain Relieving Stick

Active ingredient:

Menthol 15%

Purpose:

Pain Relieving Stick

Uses

Temporarily relieves minor aches and pains of muscles and joints associated with:
■ simple backache

■ arthritis

■ strains

■ bruises

■ sprains

Warnings
For external use only.

Flammable: Keep away from excessive heat or open flame

When using this product
■ use only as directed
■ avoid contact with the eyes or on mucous membranes
■ do not apply to wounds or damaged skin
■ do not apply to irritated skin or if excessive irritation develops
■ do not bandage tightly or use with heating pad or device

Stop use and ask a doctor if
■ you experience pain, swelling or blistering of the skin
■ condition worsens, or if symptoms persist for more than 7 days or clear
up and occur again within a few days
■ arthritic pain persists for more than 10 days, or redness is present

KEEP OUT OF REACH OF CHILDREN

If pregnant or breast-feeding, ask a health professional before use.

Keep out of reach of children. If swallowed, get medical help or
contact a Poison Control Center right away.

Directions

■ adults and children 12 years of age and older: turn dial and apply a thin
film by rubbing over affected area not more than 3 to 4 times daily.
■ children under 12 years of age: consult a physician
■ wash hands after use with cool water

Other information

■ store at 20-25°C (68-77°F)
■ store in a cool dry place away from direct sunlight

Inactive ingredients

alpha-tocopherol acetate, arachidic acid, c15-19 alkane, hydrogenated
castor oil, lauric acid, linoleic acid, linolenic acid, menthyl ethylamido oxalate,
myristic acid, oleic acid, palmitic acid, paraffin, petrolatum, stearic acid

Questions or comments? 1-866-682-4639